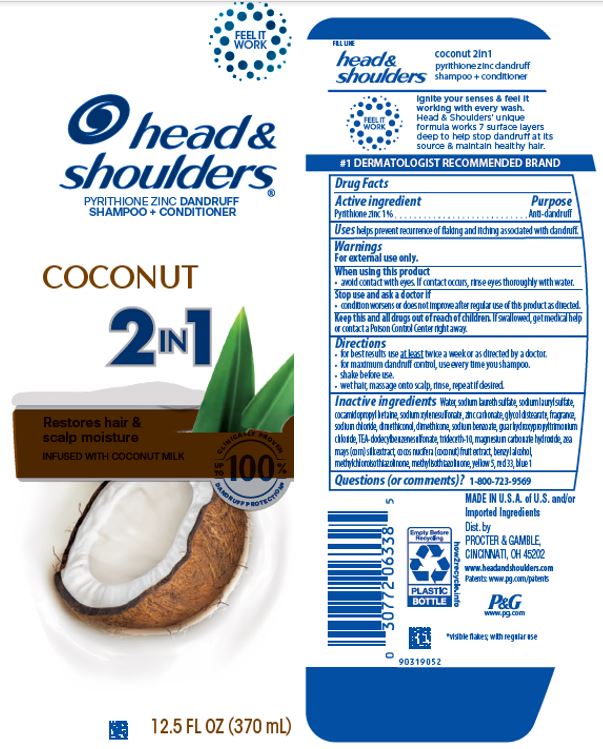 DRUG LABEL: Head and Shoulders Coconut 2in1
NDC: 69423-316 | Form: SHAMPOO
Manufacturer: The Procter & Gamble Manufacturing Company
Category: otc | Type: HUMAN OTC DRUG LABEL
Date: 20260218

ACTIVE INGREDIENTS: PYRITHIONE ZINC 1 g/100 mL
INACTIVE INGREDIENTS: GUAR HYDROXYPROPYLTRIMONIUM CHLORIDE (1.7 SUBSTITUENTS PER SACCHARIDE); FD&C YELLOW NO. 5; CORN SILK; FD&C BLUE NO. 1; WATER; SODIUM LAURETH-3 SULFATE; SODIUM LAURYL SULFATE; DIMETHICONE; ZINC CARBONATE; GLYCOL DISTEARATE; SODIUM XYLENESULFONATE; COCAMIDOPROPYL BETAINE; SODIUM CHLORIDE; SODIUM BENZOATE; MAGNESIUM CARBONATE HYDROXIDE; COCONUT; METHYLCHLOROISOTHIAZOLINONE; METHYLISOTHIAZOLINONE; D&C RED NO. 33; DIMETHICONOL (50000 CST); BENZYL ALCOHOL; TRIETHANOLAMINE DODECYLBENZENESULFONATE; TRIDECETH-10

Head and Shoulders® Coconut 2in1

Drug Facts

Active ingredient

Pyrithione zinc 1%

Purpose

Anti-dandruff

Uses

helps prevent recurrence of flaking and itching associated with dandruff.

Warnings

For external use only.

When using this product

- avoid contact with eyes. If contact occurs, rinse eyes thoroughly with water.

Stop use and ask a doctor if

- condition worsens or does not improve after regular use of this product as directed.

KEEP OUT OF REACH OF CHILDREN

Keep this and all drugs out of reach of children. If swallowed, get medical help or contact a Poison Control Center right away.

Directions

- for best results use at least twice a week or as directed by a doctor.
- for maximum dandruff control, use every time you shampoo.
- shake before use.
- wet hair, massage onto scalp, rinse, repeat if desired.

Inactive ingredients

Water, sodium laureth sulfate, sodium lauryl sulfate, cocamidopropyl betaine, sodium xylenesulfonate, zinc carbonate, glycol distearate, fragrance, sodium chloride, dimethiconol, dimethicone, sodium benzoate, guar hydroxypropyltrimonium chloride,TEA-dodecylbenzenesulfonate, trideceth-10,magnesium carbonate hydroxide, zea mays (corn) silk extract, cocos nucifera (coconut) fruit extract, benzyl alcohol, methylchloroisothiazolinone, methylisothiazolinone, yellow5, red 33, blue 1

Questions (or comments)?

1-800-723-9569

Dist. by PROCTER & GAMBLE,
CINCINNATI, OH 45202

PRINCIPAL DISPLAY PANEL - 370 mL Bottle Label

head &
shoulders ®

pyrithione zinc dandruff

shampoo + conditioner

COCONUT

2in1

RESTORES HAIR & SCALP MOISTURE

INFUSED WITH COCONUT MILK

FLAKE FREE.*
UP TO 100%
GUARANTEED

12.5 FL OZ (370 mL)